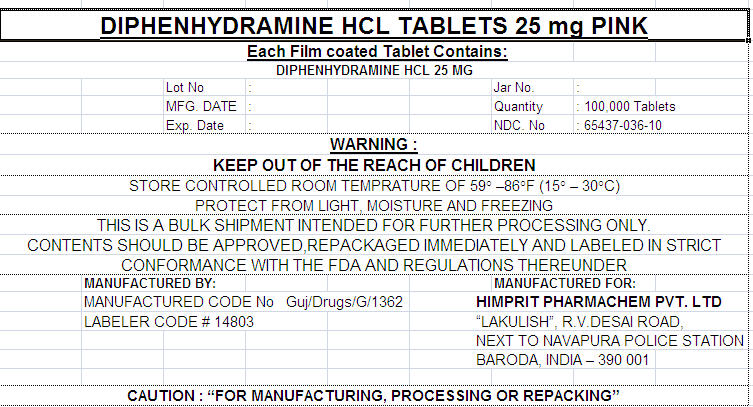 DRUG LABEL: DIPHENHYDRAMINE HYDROCHLORIDE
NDC: 65437-036 | Form: TABLET, FILM COATED
Manufacturer: HIMPRIT PHARMACHEM PVT LTD
Category: otc | Type: HUMAN OTC DRUG LABEL
Date: 20100203

ACTIVE INGREDIENTS: DIPHENHYDRAMINE HYDROCHLORIDE 25 mg/1 1
INACTIVE INGREDIENTS: CELLULOSE, MICROCRYSTALLINE; SILICON DIOXIDE; ANHYDROUS DIBASIC CALCIUM PHOSPHATE; CROSCARMELLOSE SODIUM; MAGNESIUM STEARATE; POLYETHYLENE GLYCOL; POLYVINYL ALCOHOL; TITANIUM DIOXIDE; WATER; D&C RED NO. 27

DIPHENHYDRAMINE HCL TABLETS 25 mg PINK

Drug Facts

Active ingredient (in each tablet)

Diphenhydramine HCl 25 mg

Purpose

Antihistamine

Uses

- temporarily relieves these symptoms due to hay fever or other upper respiratory allergies:
  - runny nose
  - sneezing
  - itchy, watery eyes
  - itching of the nose or throat
- temporarily relieves these symptoms due to the common cold:
  - runny nose
  - sneezing

Warnings

Do not use with any other product containing diphenhydramine, even one used on skin

Ask a doctor before use if you have

- glaucoma
- a breathing problem such as emphysema or chronic bronchitis
- trouble urinating due to an enlarged prostate gland

Ask a doctor or pharmacist before use if you are taking sedatives or tranquilizers

When using this product

- marked drowsiness may occur
- alcohol, sedatives, and tranquilizers may increase drowsiness
- be careful when driving a motor vehicle or operating machinery
- avoid alcoholic drinks
- excitability may occur, especially in children

PREGNANCY OR BREAST FEEDING

If pregnant or breast-feeding, ask a health professional before use.

Keep out of reach of children.

Directions

- take every 4 to 6 hours
- do not take more than 6 times in 24 hours

adults and children 12 years and over | 1 to 2 tablets
children 6 to under 12 years | 1 tablet
children under 6 years | do not use this product in children under 6 years of age

PRINCIPAL DISPLAY PANEL - 25 mg Label

DIPHENHYDRAMINE HCL TABLETS 25 mg PINK
Each Film coated Tablet Contains:
DIPHENHYDRAMINE HCL 25 MG

Lot No | : |  |  | Jar No. | :
MFG. DATE | : |  |  | Quantity | : 100,000 Tablets
Exp. Date | : |  |  | NDC. No | : 65437-036-10

WARNING :
KEEP OUT OF THE REACH OF CHILDREN
STORE CONTROLLED ROOM TEMPRATURE OF 59° –86°F (15° – 30°C)
PROTECT FROM LIGHT, MOISTURE AND FREEZING
THIS IS A BULK SHIPMENT INTENDED FOR FURTHER PROCESSING ONLY.
CONTENTS SHOULD BE APPROVED,REPACKAGED IMMEDIATELY AND LABELED IN STRICT
CONFORMANCE WITH THE FDA AND REGULATIONS THEREUNDER

MANUFACTURED BY:
MANUFACTURED CODE No Guj/Drugs/G/1362
LABELER CODE # 14803

MANUFACTURED FOR:
HIMPRIT PHARMACHEM PVT. LTD
"LAKULISH", R.V.DESAI ROAD,
NEXT TO NAVAPURA POLICE STATION
BARODA, INDIA – 390 001

CAUTION : "FOR MANUFACTURING, PROCESSING OR REPACKING"